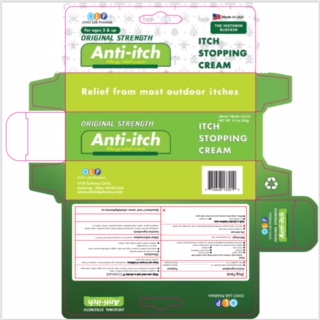 DRUG LABEL: OLP ANTI-ITCH ALLERGY RELIEF
NDC: 70648-133 | Form: CREAM
Manufacturer: OHIO LAB PHARMA LLC.
Category: otc | Type: HUMAN OTC DRUG LABEL
Date: 20181126

ACTIVE INGREDIENTS: DIPHENHYDRAMINE HYDROCHLORIDE 10 mg/1 g; ZINC ACETATE 1 mg/1 g
INACTIVE INGREDIENTS: WATER; PROPYLPARABEN; METHYLPARABEN; DECYL OLEATE; SODIUM CETOSTEARYL SULFATE; TROLAMINE; PROPYLENE GLYCOL; CETOSTEARYL ALCOHOL; EDETATE DISODIUM; STEARIC ACID; .ALPHA.-TOCOPHEROL

ACTIVE INGREDIENTS

Diphenhydramine hydrochloride 1%

Zinc Acetate 0.1%

PURPOSE

Topical analgesic

skin protectant

Uses

temporarily relieves pain and itching associated with:

- insect bites
- minor burns
- sunburn
- minor skin irritations
- minor cuts
- scrapes
- rashes due to poison ivy, poison oak, and poison sumac
- dries the oozing and weeping of poison ivy, poison oak and poison sumac

warnings

For external use only.

do not use

- on large areas of the body
- with any other product containing diphenhydramine, even one taken by mouth

Ask a doctor before use

- on chicken pox
- on measles

When using this product avoid contact with eyes

Stop use and ask a doctor if

- condition worsens or does not improve within 7 days
- symptoms persist for more than 7 days or clear up and occur again within a few days

Keep out of reach of children. If swallowed, get medical help or contact a Poison Control Center right away.

Directions

- do not use more than directed
- adults and children 2 years of age and older: apply to affected area not more than 3 to 4 times daily
- children under 2 years of age: ask a doctor

Other information

protect from excessive heat (40°C/104°F)

inactive ingredients

cetostearyl alcohol, sodium cetostearyl sulfate, stearic acid, trolamine, decyl oleate, propylene glycol, water, methyl paraben, propyl paraben, EDTA, vitamin E

Questions

www.ohiolabpharma.us

PACKAGE LABEL

Net weight 20 g

NDC#70648-133-01